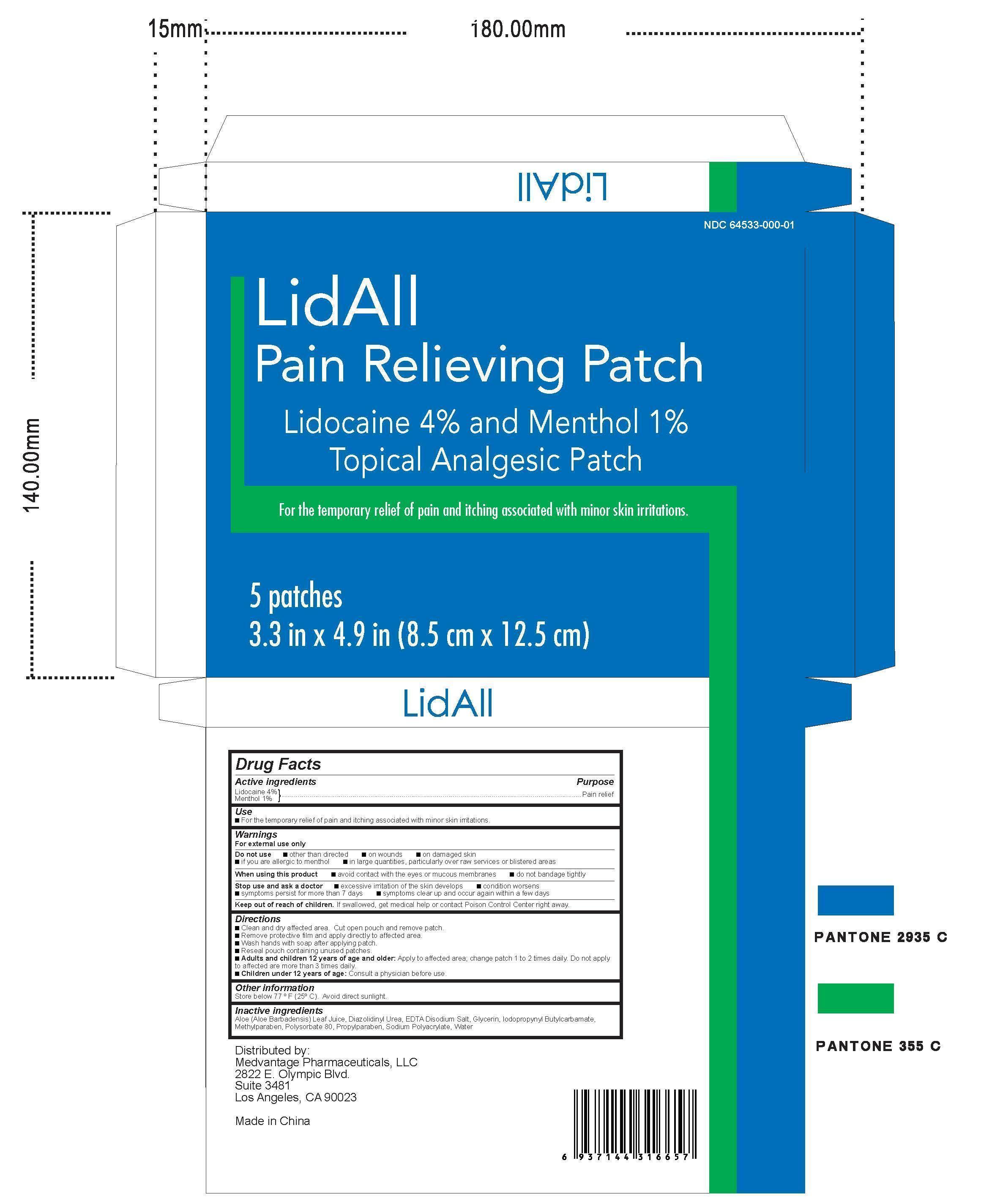 DRUG LABEL: LidAll
NDC: 64533-000 | Form: PATCH
Manufacturer: MedVantage Pharmaceutical, LLC
Category: otc | Type: HUMAN OTC DRUG LABEL
Date: 20140429

ACTIVE INGREDIENTS: LIDOCAINE 4 g/100 g; MENTHOL 1 g/100 g
INACTIVE INGREDIENTS: ALOE; DIAZOLIDINYL UREA; EDETIC ACID; EDETATE DISODIUM; GLYCERIN; IODOPROPYNYL BUTYLCARBAMATE; METHYLPARABEN; POLYSORBATE 80; PROPYLPARABEN; SODIUM POLYACRYLATE (8000 MW); WATER

LidAll Pain Relieving Patch

Warnings

For external use only

Do not use

■ other than directed

■ on wounds

■ on damaged skin

■if you are allergic to menthol

■ in large quantities, particularly over raw services or blistered areas

When using this product

■ avoid contact with the eyes or mucous membranes

■ do not bandage tightly

Stop use and ask a doctor

■ excessive irritation of the skin develops

■ condition worsens

■symptoms persist for more than 7 days

■ symptoms clear up and occur again within a few days

Active ingredients

Lidocaine 4%

Menthol 1%

Inactive ingredients

Aloe (Aloe Barbadensis) Leaf Juice, Diazolidinyl Urea, EDTA Disodium Salt, Glycerin, Iodopropynyl Butylcarbamate,

Methylparaben, Polysorbate 80, Propylparaben, Sodium Polyacrylate, Water

Keep out of reach of children.

If swallowed, get medical help or contact Poison Control Center right away.

Directions

■Clean and dry affected area. Cut open pouch and remove patch.

■Remove protective film and apply directly to affected area.

■Wash hands with soap after applying patch.

■Reseal pouch containing unused patches.

■Adults and children 12 years of age and older: Apply to affected area; change patch 1 to 2 times daily. Do not apply

to affected are more than 3 times daily.

■Children under 12 years of age: Consult a physician before use.

Purpose

Pain relief

Use

■For the temporary relief of pain and itching associated with minor skin irritations.

Other information

Store below 77 º F (25º C). Avoid direct sunlight.